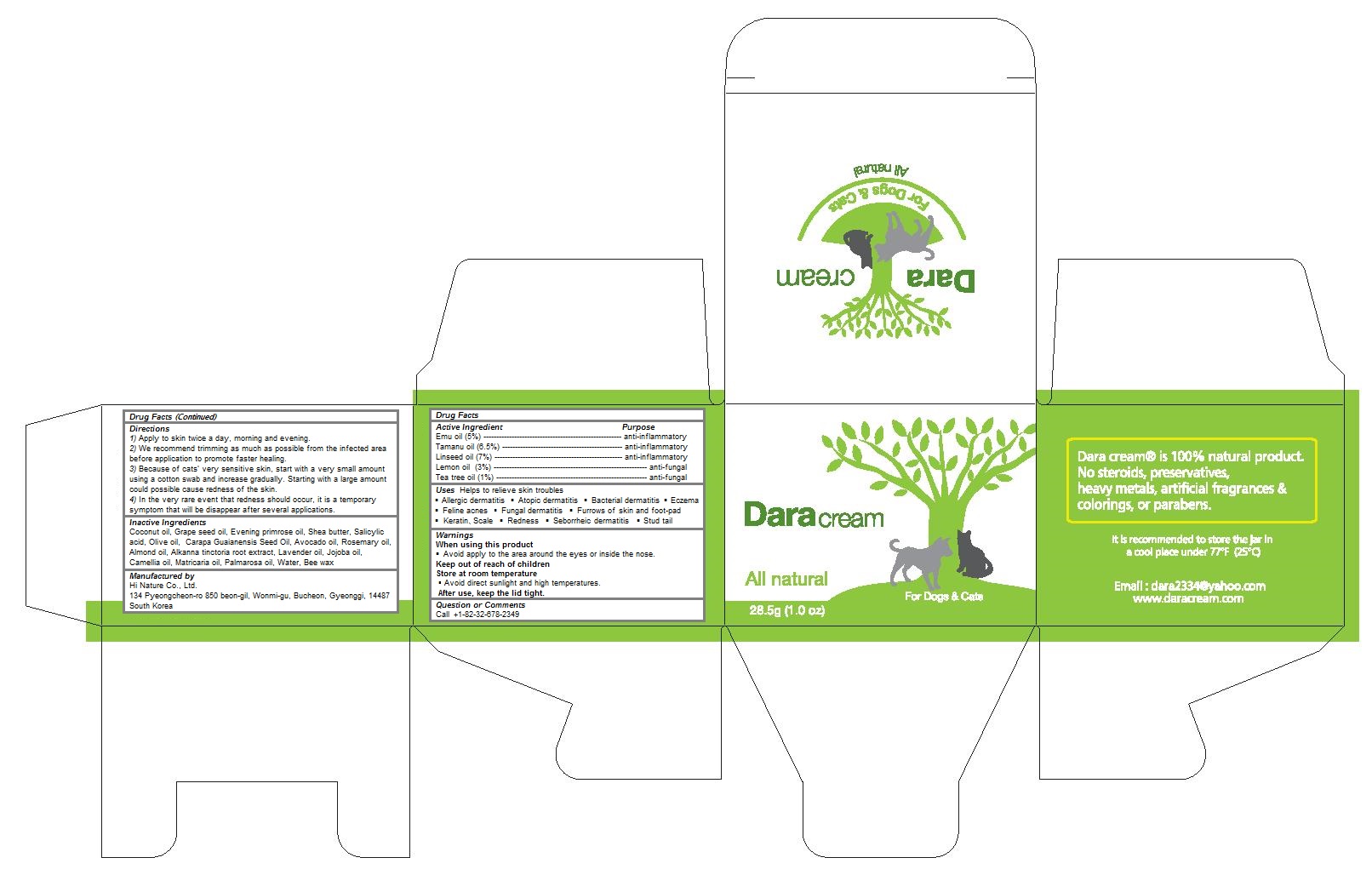 DRUG LABEL: Dara Cream (28.5g)
NDC: 86068-101 | Form: CREAM
Manufacturer: Hi Nature Co., Ltd.
Category: animal | Type: OTC ANIMAL DRUG LABEL
Date: 20160708

ACTIVE INGREDIENTS: EMU OIL 0.05 1/23.5 g; LEMON OIL 0.03 1/23.5 g; TEA TREE OIL 0.01 1/23.5 g; TAMANU OIL 0.065 1/23.5 g; LINSEED OIL 0.07 1/23.5 g
INACTIVE INGREDIENTS: COCONUT OIL; GRAPE SEED OIL; EVENING PRIMROSE OIL; SHEA BUTTER; SALICYLIC ACID; OLIVE OIL; CARAPA GUIANENSIS SEED OIL; AVOCADO OIL; ROSEMARY OIL; ALMOND OIL; ALKANNA TINCTORIA ROOT; LAVENDER OIL; JOJOBA OIL; CAMELLIA OIL; CHAMOMILE FLOWER OIL; PALMAROSA OIL; water; YELLOW WAX

Dara Cream (28.5g)